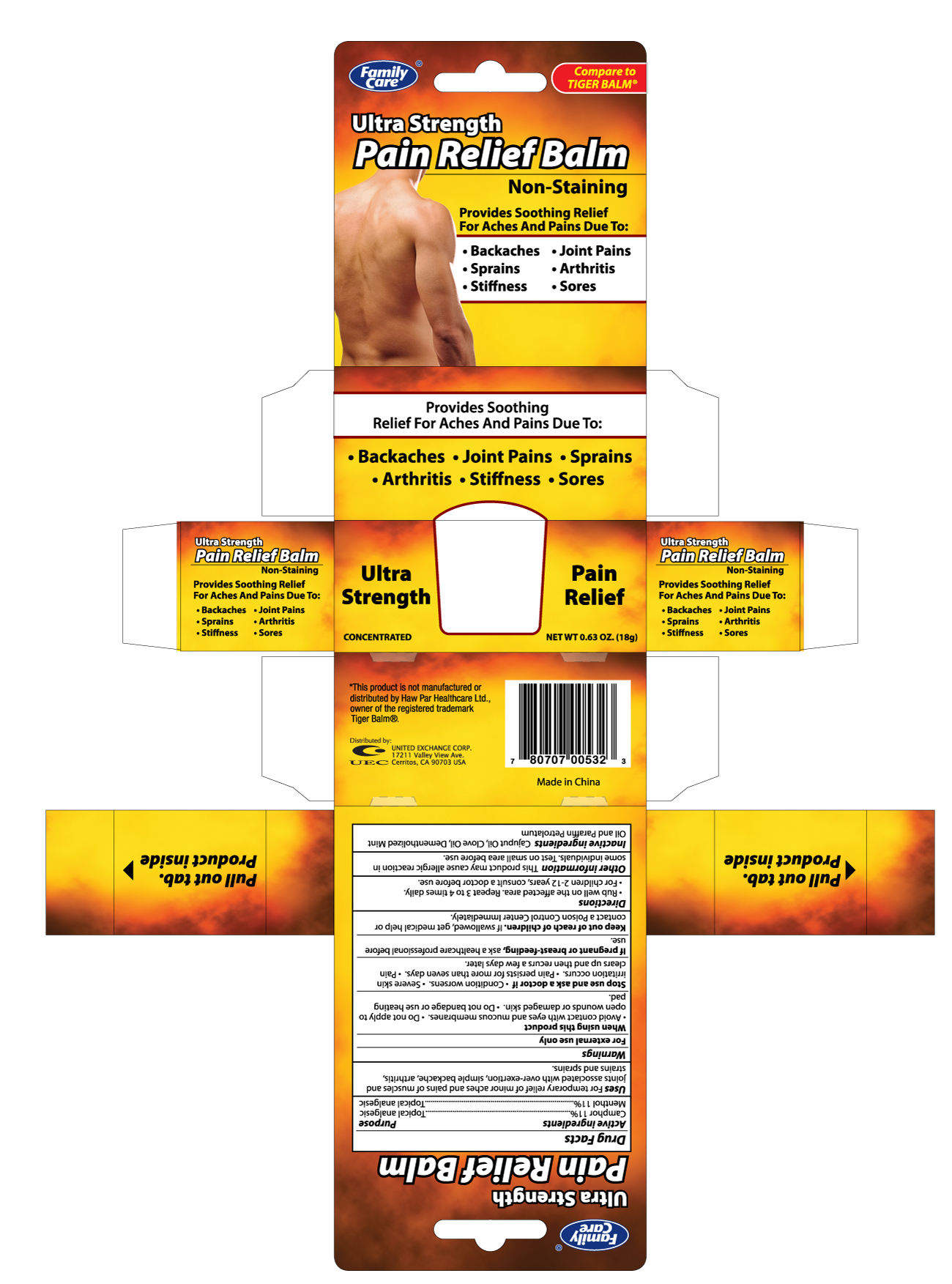 DRUG LABEL: FAMILY CARE ULTRA STRENGTH PAIN RELIEF
NDC: 65923-008 | Form: OINTMENT
Manufacturer: UNITED EXCHANGE CORP.
Category: otc | Type: HUMAN OTC DRUG LABEL
Date: 20120214

ACTIVE INGREDIENTS: CAMPHOR (SYNTHETIC) 110 mg/1 g; MENTHOL 110 mg/1 g
INACTIVE INGREDIENTS: CAJUPUT OIL; CLOVE OIL

Drug Facts

Active ingredients Purpose

Camphor 11% ...........................................................................Topical analgesic

Menthol 11% ............................................................................Topical analgesic

Uses

For temporary relief of minor aches and pains of muscles and joints associated with over-exertion, simple backache, arthritis, strains and sprains.

Warnings

For external use only

When using this product

- Avoid contact with eyes and mucous membranes
- Do not apply to open wounds or damaged skin
- Do not bandage or use heating pad

Stop use and ask a doctor if

- Condition worsens
- Severe skin irritation occurs
- Pain persists for more than seven days
- Pain clears up and then recurs few days later

PREGNANCY OR BREAST FEEDING

If pregnant or breast-feeding, ask a healthcare professional before use.

Keep out of reach of children.

If swallowed, get medical help or contact a Poison Control Center immediately.

Directions

- Rub well on the affected area. Repeat 3 to 4 times daily.
- For children 2-12 years, consult a doctor before use.

Other information

This product may cause allergic reaction in some individuals. Test on small area before use.

Inactive ingredients

Cajuput Oil, Clove Oil, Dementholized Mint Oil and Paraffin Petrolatum

DOSAGE AND ADMINISTRATION

Distributed by:

UNITED EXCHANGE CORP.

17211 VALLEY VIEW AVE.

CERRITOS, CA 90703 USA

Made in China

PACKAGE LABEL

Enter section text here